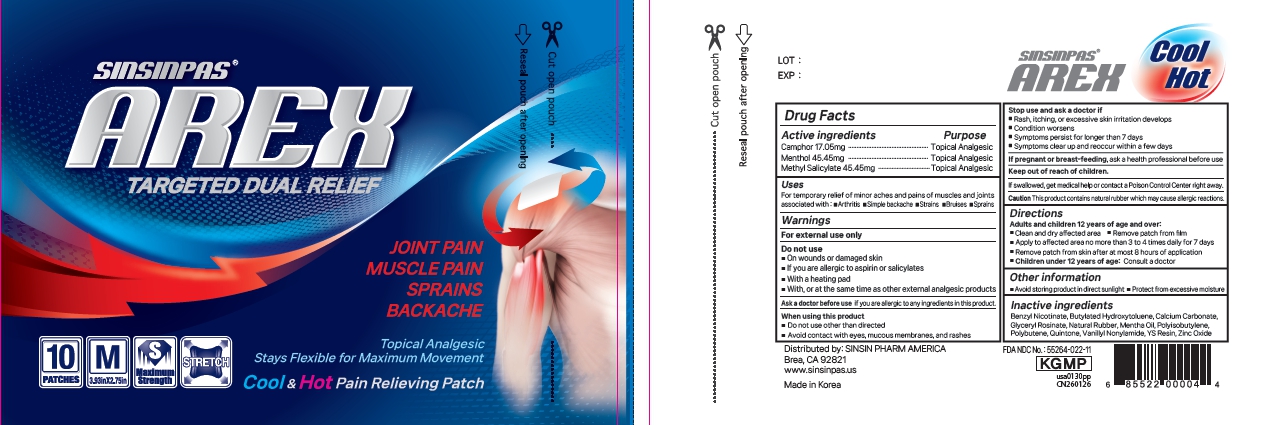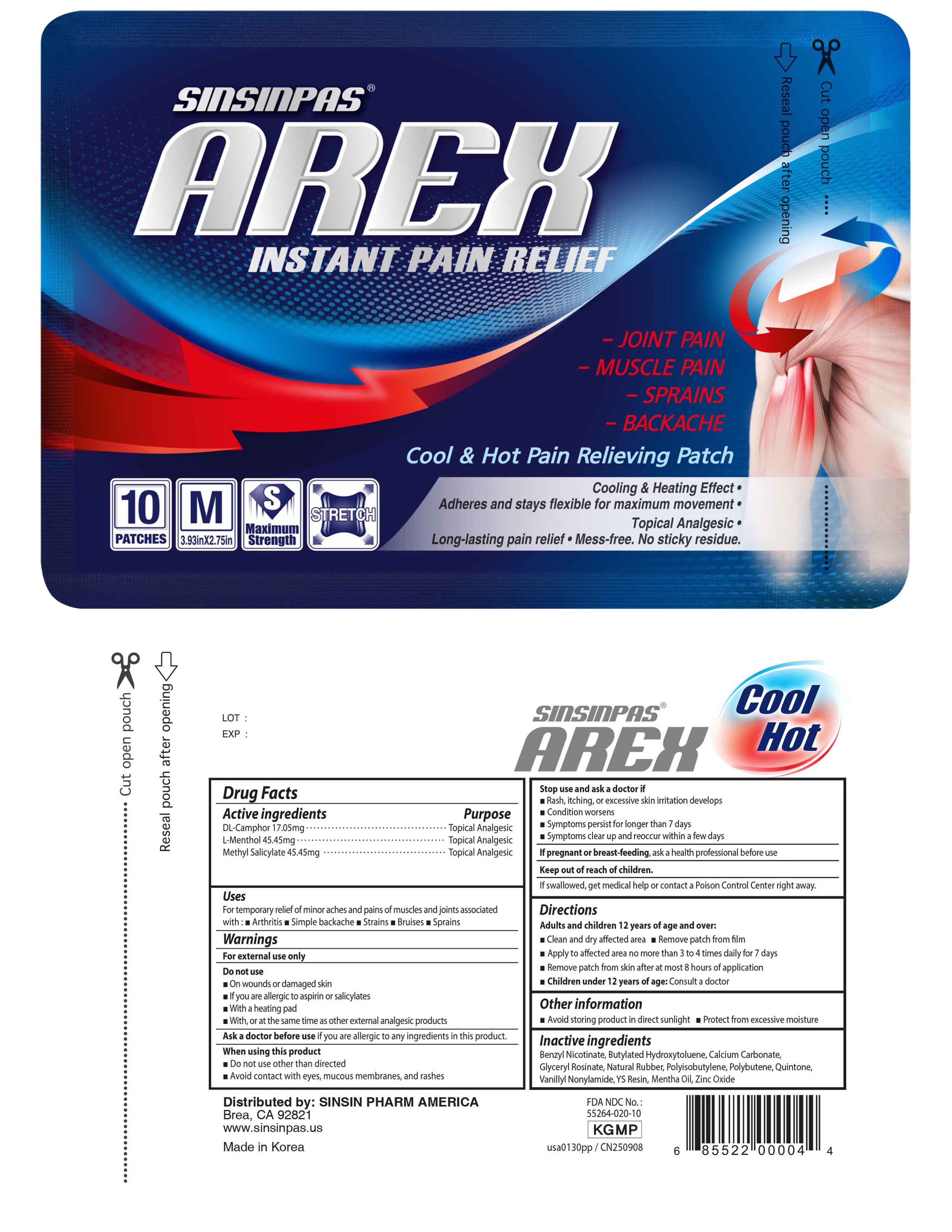 DRUG LABEL: Sinsinpas Arex Pain Relieving Patch, Medium
NDC: 55264-022 | Form: PATCH
Manufacturer: Sinsin Pharmaceutical Co., Ltd.
Category: otc | Type: HUMAN OTC DRUG LABEL
Date: 20260220

ACTIVE INGREDIENTS: LEVOMENTHOL 45.45 mg/1 1; METHYL SALICYLATE 45.45 mg/1 1; CAMPHOR (SYNTHETIC) 17.05 mg/1 1
INACTIVE INGREDIENTS: GLYCERIN; BUTYLATED HYDROXYTOLUENE; POLYISOBUTYLENE (200000 MW); ROSIN; CALCIUM CARBONATE; PEPPERMINT OIL; NONIVAMIDE; ZINC OXIDE; BENZYL NICOTINAMIDE; NATURAL LATEX RUBBER; POLYBUTENE (1400 MW)

ACTIVE INGREDIENT

DL-Camphor 17.05 mg
L-Menthol 45.45 mg
Methyl Salicylate 45.45 mg

PURPOSE

Topical Analgesic

INDICATIONS AND USAGE

For temporary relief of minor aches and pains of muscles and joints associated with:
arthritis
simple backache
strains
bruises
sprains

WARNINGS

For external use only

DO NOT USE

on wounds or damaged skin
if you are allergic to aspirin or salicylates
with a heating pad
with, or at the same time as, other external analgesic products.

PREGNANCY OR BREAST FEEDING

If pregnant and/or breast feeding, ask a health professional before use

Stop use and ask a doctor if

Rash, itching, or excessive skin irritation develops
Condition worsens
Symptoms persist for longer than 7 days
Symptoms clear up and reoccur within a few days

When using this product

Do not use other than directed
Avoid contact with eyes, mucous membranes, and rashes

WARNINGS AND PRECAUTIONS

This product contains natural rubber which may cause allergic reactions.

DOSAGE AND ADMINISTRATION

Adults and children 12 years of age and over:
Clean and dry affected area
Remove patch from film.
Apply to affected area not more than 3 to 4 times daily for 7 days.
Remove patch from skin after at most 8 hours application.

Children under 12 years of age:
Consult a doctor.

STORAGE AND HANDLING

- avoid storing product in direct sunlight
- protect from excessive moisture

INACTIVE INGREDIENT

Mentha Oil, Zinc Oxide, Benzyl Nicothinamide, Butylated Hydroxytoluene, Calcium Carbonate, Glyceryl Rosinate, Natural Rubber, Polyisobutylene, Polybutene, Quintone, Vanillyl Nonylamide, YSResin.

Manufactured by:

SINSIN PHARM. CO., LTD.

Keep out of reach of children